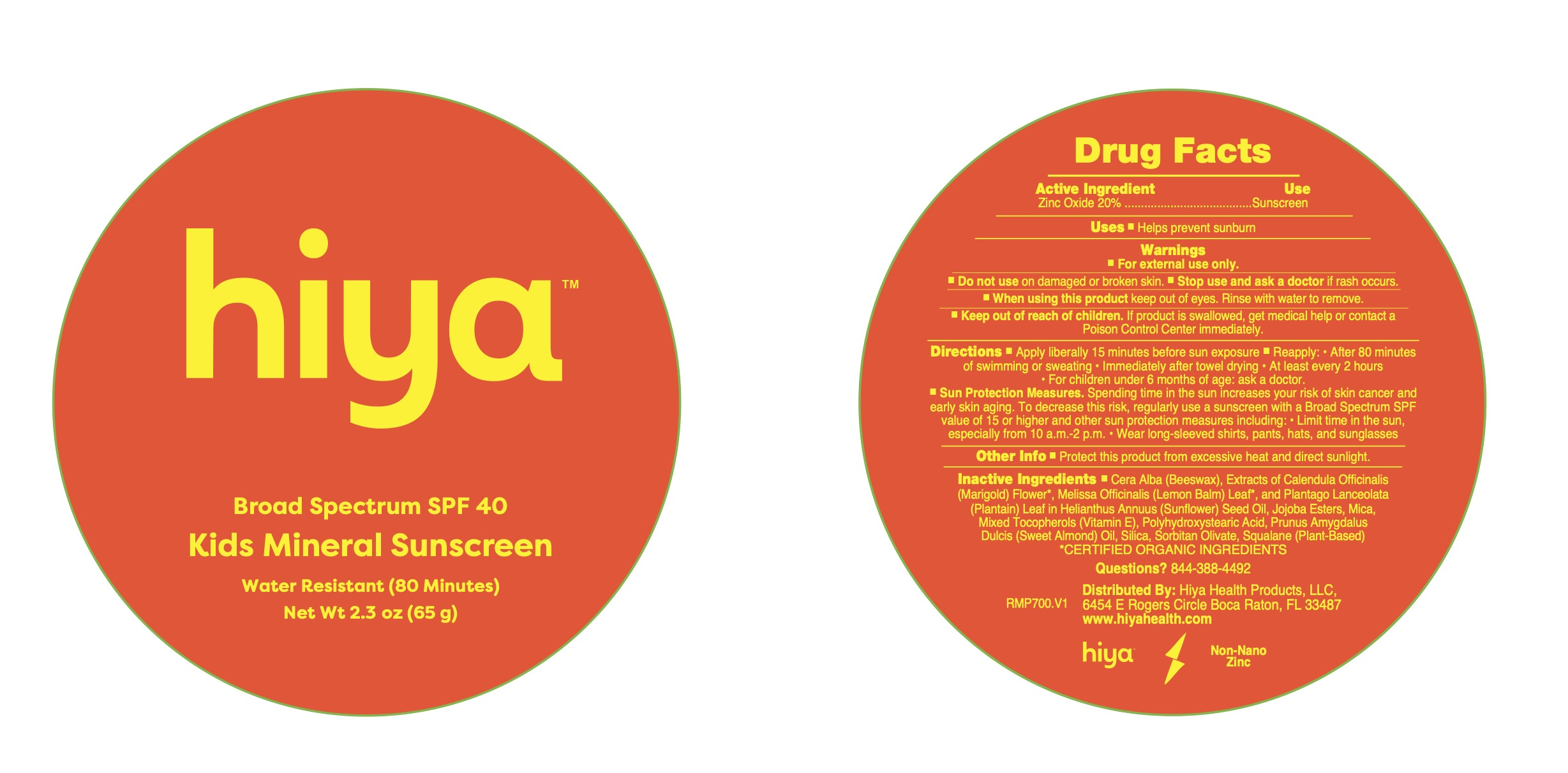 DRUG LABEL: Hiya Kids SPF 40 Mineral Sunscren
NDC: 85447-001 | Form: PASTE
Manufacturer: Hiya Health Products LLC
Category: otc | Type: HUMAN OTC DRUG LABEL
Date: 20250501

ACTIVE INGREDIENTS: ZINC OXIDE 200 mg/1 g
INACTIVE INGREDIENTS: POLYHYDROXYSTEARIC ACID (2300 MW); PRUNUS AMYGDALUS DULCIS (SWEET ALMOND) OIL; BEESWAX; HYDROLYZED JOJOBA ESTERS; .ALPHA.-TOCOPHEROL ACETATE; LEMON BALM OIL; SORBITAN OLIVATE; CALENDULA OFFICINALIS FLOWER; MICA; PLANTAGO LANCEOLATA LEAF; SILICA; SUNFLOWER OIL; SQUALANE

ACTIVE INGREDIENT

Zinc Oxide 20%

PURPOSE

Sunscreen

INDICATIONS AND USAGE

Helps prevent sunburn.

WARNINGS

For external use only.

Do not use on damaged or broken skin.

Stop use and ask a doctor if rash occurs.

When using this product keep out of eyes. Rinse with water to remove.

KEEP OUT OF REACH OF CHILDREN

If product is swallowed, get medical help or contact a Poison Control Ceenter immediately.

DOSAGE AND ADMINISTRATION

Apply liberally 15 minutes before sun exposure. Reapply after 80 minutes of swimming or sweating, immediately after towel drying, at least every 2 hours.

For children under 6 months of age: ask a doctor.

Sun Protection Measures. Spending time in the sun increases your risk of skin cancer and early skin aging. To decrease this risk, regularly use a sunscreen with a Broad Spectrum SPF value of 15 or higher and other sun protection measures including: limit time in the sun, especially from 10 am - 2 pm. Wear long-sleeved shirts, pants, hats, and sunglasses.

INACTIVE INGREDIENT

Cera Alba (Beeswax), Extracts of Calendula Officinalis (Marigold) Flower*, Melissa Officinalis (Lemon Balm) Leaf* and Pantago Lanceolata (Plantain) Leaf in Healianthus Annuus (Sunflower) Seed Oil, Jojoba Esters, Mica, Mixed Tocopherols (Vitamin E), Polyhydroxystearic Acid, Prunus Amygdalus Dulcis (Sweet Almond) Oil, Silica, Sorbitan Olivate, Squalan (Plant-Based) *Certified Organic Ingredients.